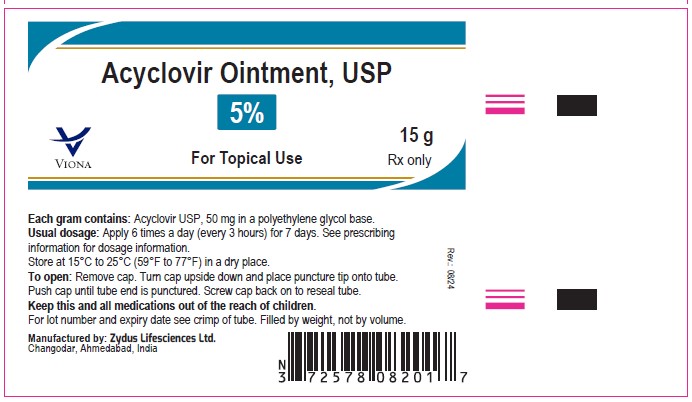 DRUG LABEL: acyclovir
NDC: 70771-1371 | Form: OINTMENT
Manufacturer: Zydus Lifesciences Limited
Category: prescription | Type: HUMAN PRESCRIPTION DRUG LABEL
Date: 20240814

ACTIVE INGREDIENTS: ACYCLOVIR 50 mg/1 g
INACTIVE INGREDIENTS: POLYETHYLENE GLYCOL, UNSPECIFIED

Acyclovir Ointment USP, 5%

PACKAGE LABEL

Acyclovir Ointment USP, 5%

NDC 70771-1371-1 in tube of 15 gm

Rx Only